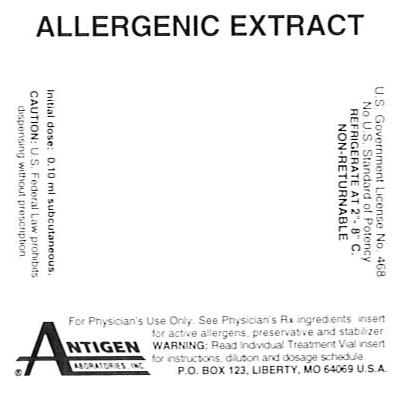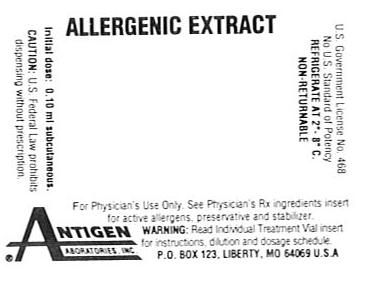 DRUG LABEL: Treatment Set TS350663
NDC: 49288-0943 | Form: INJECTION, SOLUTION
Manufacturer: Antigen Laboratories, Inc.
Category: other | Type: NON-STANDARDIZED ALLERGENIC LABEL
Date: 20130604

ACTIVE INGREDIENTS: AMBROSIA ARTEMISIIFOLIA POLLEN 4000 [AU]/1 mL; CYNODON DACTYLON POLLEN 400 [BAU]/1 mL; FESTUCA PRATENSIS POLLEN 4000 [BAU]/1 mL; PHLEUM PRATENSE POLLEN 4000 [BAU]/1 mL; PASCOPYRUM SMITHII POLLEN 0.002 g/1 mL; CANIS LUPUS FAMILIARIS HAIR 0.002 g/1 mL; PERIPLANETA AMERICANA 0.002 g/1 mL; DERMATOPHAGOIDES PTERONYSSINUS 400 [AU]/1 mL; ALTERNARIA ALTERNATA 0.002 g/1 mL; ASPERGILLUS FUMIGATUS 0.002 g/1 mL; COCHLIOBOLUS SATIVUS 0.002 g/1 mL; BETULA POPULIFOLIA POLLEN 0.002 g/1 mL; POPULUS DELTOIDES POLLEN 0.002 g/1 mL; ULMUS AMERICANA POLLEN 0.002 g/1 mL; POPULUS NIGRA POLLEN 0.001 g/1 mL; POPULUS ALBA POLLEN 0.001 g/1 mL
INACTIVE INGREDIENTS: WATER; PHENOL; GLYCERIN; SODIUM BICARBONATE; SODIUM CHLORIDE

ALLERGENIC EXTRACTS
INDIVIDUAL TREATMENT VIAL

WARNINGS

Individual allergenic extract treatment vial is intended for use by physicians who are experienced in the administration of allergenic extracts for immunotherapy and the emergency care of anaphylaxis, or for use under the guidance of an allergy specialist. Individual allergenic extract treatment vials are not directly interchangeable with other allergenic extracts. The initial dose must be based on skin testing as described in the dosage and administration section of this insert. Patients being switched from other types of extract to individual treatment vials should be started as though they were coming under treatment for the first time. Patients should be instructed to recognize adverse reaction symptoms and cautioned to contact the physician's office if reaction symptoms occur. As with all allergenic extracts, severe systemic reactions may occur. In certain individuals, these reactions may be life-threatening. Patient should be observed for at least 20 minutes following treatment and emergency measures as well as personnel trained in their use should be immediately available in the event of a life-threatening reaction.

This product should not be injected intravenously. Deep subcutaneous routes have proven to be safe. See the warnings, precautions, adverse reactions and overdosage sections below.

DESCRIPTION

Allergenic extract in this vial is referred to as an individual treatment vial since it is designed primarily for the physician equipped to complete skin testing and supervise allergenic extract immunotherapy. The extract is sterile and intended for subcutaneous injection. The concentration of allergenic extract supplied will be based on the individual physician's prescription order and will be expressed in most cases on a weight/volume basis (or AU/ml with standardized extract) diluted either 1:10 or 1:5. Where mixtures of pollens and non-pollens have been ordered, the ingredients are listed on the final container label. To insure maximum potency for the entire dating period, dilutions will be prepared with 50% v/v glycerine unless otherwise specified.

Ingredients - Active allergens, preservative and stabilizer are noted on the Physicians Prescription Ingredients Insert enclosed with each individual allergenic extract treatment vial.

Dating Period - A twelve month dating period (expiration date) for the prescription vial will be on the container label. Extract Treatment Sets should be reordered when outdated. Government requirements include a two week holding period for sterility tests. Please allow three weeks minimum for delivery.

CLINICAL PHARMACOLOGY

The mechanisms by which immunotherapy (hyposensitization) is achieved are not completely understood. Anaphylaxis or "anaphylactic shock," and hay fever are caused by the same basic process: the production of IgE antibody, its attachment to mast cells and, on renewed contact with the same antigen explosive degranulation of the mast cells and release of mediators, which act on smooth muscle, mucous glands, and blood vessels. With massive release there is bronchospasm, vomiting, skin rashes, edema of the nose and throat, and vascular collapse, sometimes fatal, while with more localized release one or more of these symptoms predominates, depending on the site (tissue shock organ) of exposure to the antigen.

Antigens that can trigger these reactions are known as "allergens"; they have very diverse origins but a curious similarity of molecular weight. People who suffer unduly from allergy are called "atopic"; this trait is usually inherited and has been attributed to a variety of constitutional abnormalities.

The IgE dependent degranulation of mast cells is initiated by the bridging of pairs of cell-bound IgE by antigen and terminates rapidly. Bridging results in alteration of the cell membrane, which is associated with increased energy dependent entry of calcium, alterations in phospholipid metabolism and increase of cyclic adenosine monophosphate (cyclic AMP).

The mast cell membrane is ruffled and possesses receptors both for the Fc portion of IgE and C3b. Receptors for anaphylatoxin (C3a and C5a), have been defined functionally. In addition to IgE antigen interaction and stimulation by anaphylatoxin, mast cells may be degranulated by non-immunological stimuli such as enzymes, ionophores, polycations, radio-contrast dyes and opiates. Atopic individuals develop their symptoms principally as a result of IgE-dependent processes; however, non- IgE mediated mechanisms for the release of mast cell mediators provide additional potential for recruitment of mediators.

Subsequent to activation, the secretion of granules is under cyclic nucleotide regulation. Of direct relevance is the possibility that the mast cell itself, by histamine (H^2) and prostaglandins (E^2, D^2, I^2) may increase cyclic AMP and inhibit secretion. Conversely histamine (H^1) could elevate cyclic GMP and PGF, 2 alpha lower cyclic AMP, augmenting the release of mediators. 18

INDICATIONS AND USAGE

When the natural exposure to elevated aeroallergens produces symptoms as described under Clinical Pharmacology, specific diagnosis and therapeutic procedures are indicated. Clearly, important clues to the cause of a person's allergic condition can be gleaned from a thorough history and careful physical examination. Diagnostic tests - in vitro or in vivo - serve only to confirm the physician's suspicions or to improve investigative skills. Specific diagnosis is especially indicated when the patient's symptoms are not controlled by medication. When immunotherapy is contemplated demonstration of sensitivity to a specific allergenic extract is necessary. An orderly approach to the use of diagnostic tests usually begins with direct skin testing. 5,6,11

THIS PRODUCT IS NOT INTENDED FOR TREATMENT OF PATIENTS WHO DO NOT MANIFEST IMMEDIATE HYPERSENSITIVITY REACTIONS TO THE ALLERGENIC EXTRACT FOLLOWING SKIN TESTING.

CONTRAINDICATIONS

There are no absolute contraindications; however, extreme caution is necessary when using diagnostic skin tests or injection treatment in highly sensitive patients, who have experienced severe symptoms or anaphylaxis by natural exposure or previous skin testing or treatment. IN THESE CASES BOTH THE POTENCY FOR SKIN TESTS AND THE ESCALATION OF THE TREATMENT DOSE MUST BE ADJUSTED TO THE PATIENT’S SENSlTIVITY AND TOLERANCE.

This product is not intended for the treatment of patients who do not experience allergic symptoms upon natural exposure to the allergen. At the present time there has been no demonstrated adverse effects on the fetus when allergenic extract immunotherapy is administered during gestation to pregnant women.

100,000 AU/ml standardized allergenic extract should be used by physicians with experience in maximal dose immunotherapy and treatment of anaphylaxis.

WARNINGS

Epinephrine 1:1000 should be available.

When changing immunotherapy from an unstandardized to an AU/ml standardized allergenic extract, dose adjustment, if indicated, should be based on the comparative potency of the extracts. Patient re-evaluation may be necessary.

Injections should never be given intravenously. A 5/8 inch 25 gauge needle on a sterile syringe will allow deep subcutaneous injection. Precaution of withdrawing the plunger slightly after inserting the needle is advisable to determine if a blood vessel has been entered. Proper measurement of the dose and caution in making the injection will minimize reactions. Patients should be detained for twenty to thirty minutes after injection or advised to return to the office immediately if symptoms or reactions occur.

Sensitive patients may experience severe anaphylactic reactions resulting in respiratory obstruction, shock, coma and/or death.

GENERAL PRECAUTIONS

Pregnancy Category C: There are no adequate and well controlled studies in pregnant women. Allergenic extracts should be used during pregnancy only if the potential benefit justifies the potential risk to the fetus.

Pediatric Use: Doses of allergenic extracts for children are generally the same as those for adults. The maximum volume of extract tolerated without undue pain and swelling may be less for smaller individuals and therefore the maximum dose and treatment schedule must be individualized.

Animal reproduction studies have not been conducted with allergenic extracts. It is also not known whether allergenic extracts can cause fetal harm when administered to a pregnant woman or can affect reproduction capacity. Allergenic extracts should be given to a pregnant woman only if clearly needed. 15

Refrigerate at 2-8 degrees C.

Sterile solutions, vials, syringes, etc. should be used. Aseptic technique should be observed when making dilutions, skin testing, and extracts for treatment. The usual precautions in administering allergenic extracts are necessary.

A separate autoclave sterilized or disposable syringe and needle should be used for each individual patient to prevent transmission of serum hepatitis, A.I.D.S. and other infectious agents from one person to another.

The initial dilution of allergen extract, starting dose, and progression of dosage must be carefully determined on the basis of the patient's history and results of skin tests. Patients with a history of severe sensitivity and markedly positive skin tests to high dilutions of the allergen extract should be started with low doses of highly diluted extract. Pregnancy or a history of prior reactions to allergen immunotherapy dictates the need to start with small quantities of antigen.

If the first injection of the initial dilution of extract is tolerated without significant local reaction, increasing doses by 5-20% increments of that dilution may be administered. The rate of increase in dosage in the early stages of treatment with highly diluted extracts is usually more rapid than the rate of increase possible with more concentrated extracts. This schedule is intended only as a guide and must be modified according to the reactivity of the individual patient. Needless to say, the physician must proceed cautiously in the treatment of the highly sensitive patient who develops large local or systemic reactions.

Some patients may tolerate larger doses, but it is rarely necessary to give maintenance doses larger than 2,000 AU/ml of the standardized extract or 0.5 ml of 1:100 w/v of the unstandardized extract. Because dilute extracts tend to lose activity on storage, the first dose from a more concentrated vial, should be the same or less than the previous dose.1,2,3,4,16

Immunotherapy must be given under the supervision of a physician. Before an injection is given the patient should be asked about any reaction following the previous injection to help determine the next dose. Target maintenance dose should be determined by the physician’s experience and patient response to skin testing and treatment.

Dosages progressively increase thereafter according to the tolerance of the patient at intervals of one to seven days until, (1) the patient achieves relief of symptoms, (2) induration at the site of injection is no larger than 50 mm in 36 to 48 hours, (3) a maintenance dose short of aggravating existing symptoms, systemic symptoms, or anaphylaxis. The dose should be escalated until the patient is receiving a final maintenance dose containing 2.7 to 22 u/ml or more of ragweed AgE (using Short Ragweed as example) or demonstrates untoward reactions that indicate the dose to be excessive. This maintenance dose may be continued at regular intervals perennially or achieved each year by a new, but shortened course of treatment. It may be necessary to adjust the progression of dosage downward to avoid local and constitutional reactions.

Immunotherapy of patients highly sensitive to ragweed pollen (using Short Ragweed as an example) receiving a dose of 2.7 to 46.8 units of ragweed AgE (1,000-2,000 or more AU/ml of standardized ragweed extract) was significantly more effective than placebo for (1) relieving symptoms of ragweed hay fever, (2) producing increase in serum levels of anti-ragweed IgG, (3) decrease in seasonal rises in levels of anti-ragweed IgE, (4) decrease in leukocyte histamine release from exposure to ragweed pollen extract in some patients, and (5) increase in IgG and IgA antibodies in nasal secretions. 17

In addition to these changes in humoral antibody production, immunotherapy also effects some cellular changes. Basophils from treated subjects release less histamine in vitro and are less sensitive to the allergen (that is, higher concentrations of allergens are required to induce histamine release) than are basophils from non-treated patients. Lymphocytes from treated patients exhibit decreased proliferative response and decreased production of lymphokine in the presence of the specific allergen. A state of tolerance may be induced in the IgE producing B lymphocytes, there may be impairment in T-lymphocyte helper function, or immunotherapy may generate suppressor cells. Antigen specific suppressor cells, probably bearing histamine receptors, are generated during immunotherapy for allergy and may be partly responsible for the efficacy of this therapy. 14

Loss of potency of aqueous pollen extracts has been recognized as a problem since shortly after the introduction of modern methods of immunotherapy. This loss of potency occurs more rapidly in saline extracts without added preservatives at high temperature and at greater extract dilutions. At concentrations of 1:100 all dilutions containing glycerin, human serum albumin, maintained extract potency within 1 logarithm (log) dilution of the original strength for 12 months; glycerin was significantly superior to all other extracts at 1, 3, and 12 months; and the deleterious effect of phenol was minimal. The deleterious effect of phenol was more marked at the higher dilutions. It was concluded that there may be marked loss of potency of dilute pollen extracts stored for periods of only two weeks under conditions which may be encountered in normal clinical practice. 12

DOSAGE AND ADMINISTRATION

As a consequence of the discovery of IgE and the development of methods to identify and quantify anti-allergen IgE levels, interest in recent years has centered around the utilization of in vivo and in vitro diagnostic procedures. 7,9

Patients who react to a small quantity of antigen by skin testing can be classified as highly sensitive. Those who react only to large quantities of antigen can be classified as less sensitive. It would appear that there is at least a 50,000-fold range between the most and least sensitive individuals. On the other hand, certain patients who do not appear to have elevated quantities of specific anti-allergen IgE do have positive skin tests and have symptoms of allergic rhinitis. These patients are considerably less sensitive than patients with detectable levels of specific IgE antibody. 10

The current standard method of immunotherapy dates back to the earliest studies by Noon. As adapted for ragweed pollen extract, therapy is begun with a low dose, which has been shown to be tolerated by both experience and skin testing.

The physician who undertakes immunotherapy should be concerned with the degree of sensitivity of the patient. This can be measured by skin test, leukocyte histamine release, or anti-allergen IgE levels. Strongly positive skin tests or high initial ragweed IgE and total IgE may be risk factors for systemic reactions. Less aggressive immunotherapy schedules may be indicated for such patients. Maintenance dose potency must be established by the physician's clinical observation and experience. 10,17

Serial fivefold or tenfold dilutions of the extract are used to make more dilute extract concentrations. Other concentrations can be prepared by appropriate dilution. In brief, the allergist can prepare any dilution of extract that is considered appropriate for the patient.

ADVERSE REACTIONS

Systemic reactions may range from mild exaggeration of the patient’s allergic symptoms to anaphylactic reactions. Very sensitive patients may show a rapid response. In some instances a severe systemic reaction with blood pressure fall and/or shock may occur. Quantitation of patient's sensitivity combined with careful early observation is essential for safe skin testing and treatment.

Other reactions include, but are not necessarily limited to urticaria, itching, edema of the extremities, respiratory wheezing or asthma, dyspnea, cyanosis, tachycardia, lacrimation, marked perspiration, flushing of the face, neck or upper chest, mild persistent clearing of the throat, hacking cough, or persistent sneezing.

1) Local Reactions

Small amounts of erythema and swelling at the site of injection are common, the extent varying with the patient. Such reactions should not be considered significant unless they persist for at least 24 hours or exceed 50 mm. in diameter.

Larger local reactions are not only uncomfortable, but also indicate the possibility of a systemic reaction if dosage is increased. In such cases the dosage should be reduced to the last level not causing the reaction and maintained at this level for two or three treatments before cautiously increasing again.

Large, persistent local reactions or minor exacerbations of the patient’s allergic symptoms may be treated by local cold applications and/or the use of oral antihistamines, but they should be considered a warning of possible severe systemic reactions and the need for temporarily reduced dosages.

A mild burning immediately after the injection is to be expected; this usually leaves in 10 to 20 seconds. Prolonged pain, or pain radiating up the arm, is usually the result of intramuscular injection, making this injection route undesirable. Subcutaneous injection is the recommended route.

2) Systemic Reactions

With careful attention to dosage and administration, such reactions occur infrequentIy, but it must be remembered that allergenic extracts are highly potent to sensitive individuals and OVERDOSE could result in anaphylactic symptoms. Therefore, it is imperative that physicians administering allergenic extracts understand and be prepared for the treatment of severe reactions.

Adverse reaction frequency data for allergenic extract administration is not available. Inherent difficulties in establishing such data are the wide variations in clinical allergy types, patient sensitivity, treatment schedules used by allergists, potency of extracts from various sources, etc.

It cannot be overemphasized that, under certain unpredictable combinations of circumstances, anaphylactic shock is always a possibility. Other possible systemic reaction symptoms are, in varying degrees of severity, fainting, pallor, bradycardia, hypotension, angioedema, cough, wheezing, conjunctivitis, rhinitis, and urticaria.17,18

OVERDOSAGE

If a systemic or anaphylactic reaction does occur, apply a tourniquet above the site of injection and inject intramuscularly or subcutaneously 0.3 to 0.5 ml of 1:1000 epinephrine-hydrochloride into the opposite arm. The dose may be repeated in 5-10 minutes if necessary. Loosen the tourniquet at least every 10 minutes.

The epinephrine HCL 1: 1000 dose for infants to 2 years is 0.05 to 0.1 ml; for children 2 to 6 years it is 0.15 ml; for children 6 to 12 years it is 0.2 ml.

Patients unresponsive to epinephrine may be treated with theophylline. Studies on asthmatic subjects reveal that plasma concentrations of theophylline of 5 to 20 ug/ml are associated with therapeutic effects. Toxicity is particularly apparent at concentrations greater than 20 ug/ml. A loading dose of aminophylline of 5.6 mg/kg intravenously followed by 0.9 mg/kg per hour results in plasma concentrations of approximately 10 ug/ml. (Mitenko and Ogilive 1973b; Nicholoson and Chick 1973).

Other beta-adrenergic drugs such as isoproterenol, isoetharine, or albuterol may be used by inhalation. The usual dose to relieve broncho-constriction in asthma is 0.5 ml or the 0.5% solution for isoproterenol HCL; albuterol is longer acting than isoproterenol by any route of administration. The albuterol inhaler delivers approximately 90 mcg of albuterol from the mouthpiece. The usual dosage for adults and children would be two inhalations repeated every 4 to 6 hours. Isoetharine supplied in the Bronkometer unit delivers approximately 340 mcg isoetharine. The average adult dose is one to two inhalations.

Patients receiving beta-blockers may not be responsive to epinephrine or inhaled bronchodilators. Respiratory obstruction not responding to parenteral or inhaled bronchodilators may require Theophylline, low-flow oxygen, intubation and the use of life support systems. Parenteral fluid and/or plasma expanders may be utilized for treatment of shock and low flow (two liters per minute) oxygen may be utilized if indicated. Adenocorticosteroids may be administered parenterally or intravenously. 8

HOW SUPPLIED

Individual treatment sets as prescribed by the physician. The allergenic extract contains a variable number of individual doses depending on the patient's sensitivity and maximum tolerated maintenance treatment dose.

REFERENCES

1. Baer, Harold E.: The Regulation of Allergenic Extracts by the• U.S. Food and Drug Administration, Regulatory Control and Standardization of Allergenic Extracts, First International Paul-Ehrlich Seminar, May 20-22, 1979, Frankfurt, Germany, pp. 10-11.

2. Baer, Harold E.: Evaluation of RAST Inhibition, International Joint Steering Committee for Allergen Standardization, Course on Allergen Standardization, The Protein Laboratory, University of Copenhagen, August 4-9, 1980.

3. Baer, Harold E., L. Bolin, D. Levy, H. Lowenstein, & A. DeWeck: Standard reference extracts, (round table discussion), International Joint Steering Committee for Allergen Standardization, Course on Allergen Standardization. The Protein Laboratory, University of Copenhagen, August 4-9, 1980.

4. Baer, Harold E.: Second International Paul-Ehrlich Seminar on Regulatory Control and Standardization of Allergenic Extract, Frankfurt, Germany, September 13-15, 1981.

5. Evans, Richard, III and Summers, Richard: In vivo and in vitro tests to confirm clinical findings - Diagnostic tests for allergic patients. Journal of Respiratory Diseases, Vol. 65, No. 7, July 1981.

6. Fadal, Richard G. & Nalebuff, Donald J.: Tools of the Allergists: Old and New. Continuing Education for the Family Physician, Vol. 10, No. 5, May 1979, pp. 37-61.

7. Allergenic Products: Antigen E. Potency Test: Additional Standards for Miscellaneous Products, 21 CFR Part 680, Federal Register, Vol. 46, No. 147, Friday, July 31, 1981, Rules and Regulations, pp. 39128-39136.

8. Goodman, Louis S., Gillman, Alfred: Editors, The Pharmacological Basis of Therapeutics. MacMillan Publishing Co., Inc., Chapter 19, p. 375.

9. Kniker, William T.: Clinical Science and Common Sense in the Diagnosis and Immunotherapy of Respiratory Allergy. Continuing Education for the Family Physician, Vol. 10, No. 5, May 1979, pp. 16-33.

10. Matthews, Kenneth, et al: Rhinitis, Asthma and the Other Allergic Diseases, NIAID Task Force Report, U.S. Dept. HEW, NIH Publication No. 79-387, Chapter 4, pp. 213-217, May 1979.

11. Nalebuff, Donald J. and Fadal, Richard G.: The Modified RAST Assay: An Aid in the Diagnosis and Management of Allergic Disorders. Continuing Education for the Family Physician, Vol. 10, No. 5, May 1979, pp. 64-76.

12. Nelson, Harold S.: The Effect of Preservatives and Dilution on the Deterioration of Russian Thistle (Salsola pestifer), a pollen extract. The Journal of Allergy and Clinical Immunology. Vol. 63, No. 6, pp. 417-425, June 1979.

13. Norman, Philip S., Lichtenstein, L.M., Ishizaka, K.: Diagnostic tools in ragweed hay fever. A comparison of direct skin tests IgE antibody measurements and basophil histamine release. The Journal of Allergy and Clinical Immunology. Vol. 52, 1973, pp. 210.

14. Rocklin, Ross E., Sheffer, Albert L., Grainader, Dirk K., and Melmon, Kenneth: Generation of antigen-specific suppressor cells during allergy desensitization. New England Journal of Medicine, 302: May 29, 1980, pp. 1213-1219.

15. Seebohm, Paul M., et al: Panel on Review of Allergenic Extracts, Final Report, Food and Drug Administration, March 13, 1981, pp. 9-48.

16. Stevens, E.: Cutaneous Tests, Regulatory Control and Standardization of Allergenic Extracts, First International Paul-Ehrlich Seminar, May 20-22, 1979, Frankfurt, Germany, pp. 133-138.

17. Van Metre, Thomas E., Jr., Adkinson, N. Franklin, Jr., Amodio, Frank J., Lichtenstein, Lawrence L., Mardinay, Michael R., Jr., Norman, Philip S., Rosenberg, Gary L., Sobotka, Anne K., & Valentine, Martin D.: A comparative study of the effectiveness of the Rinkel method and the current standard method of immunology for ragweed pollen hay fever. The Journal of Clinical Allergy and Immunology, Vol. 66, No. 6, p. 511, December 1980.

18. Wasserman, S.: The mast cell and the inflammatory response, The Mast Cell - its role in health and disease. Edited by J. Pepys & A.M. Edwards, Proceedings of an International Symposium, Davos, Switzerland, Pitman Medical Publishing Co., 1979, pp. 9-20.